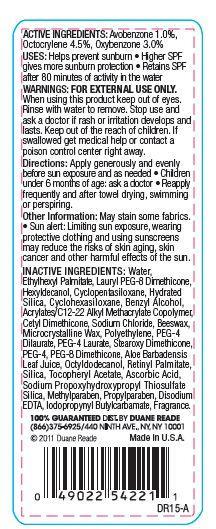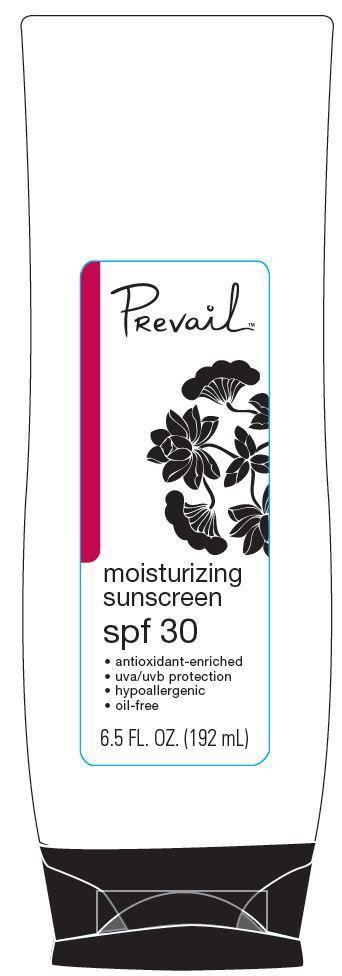 DRUG LABEL: Duane Reade Prevail Moisturizing Sunscreen
NDC: 67732-411 | Form: LOTION
Manufacturer: DUANE READE INC.
Category: otc | Type: HUMAN OTC DRUG LABEL
Date: 20121114

ACTIVE INGREDIENTS: AVOBENZONE 1 g/100 g; OCTOCRYLENE 4.5 g/100 g; OXYBENZONE 3 g/100 g
INACTIVE INGREDIENTS: WATER; ETHYLHEXYL PALMITATE; HEXYLDECANOL; CYCLOMETHICONE 5; HYDRATED SILICA; CYCLOMETHICONE 6; BENZYL ALCOHOL; SODIUM CHLORIDE; YELLOW WAX; MICROCRYSTALLINE WAX; HIGH DENSITY POLYETHYLENE; PEG-4 DILAURATE; EDETATE DISODIUM; POLYETHYLENE GLYCOL 200; PEG-8 DIMETHICONE; ALOE VERA LEAF; OCTYLDODECANOL; VITAMIN A PALMITATE; SILICON DIOXIDE; .ALPHA.-TOCOPHEROL ACETATE; ASCORBIC ACID; METHYLPARABEN; PROPYLPARABEN; IODOPROPYNYL BUTYLCARBAMATE

ACTIVE INGREDIENTS:

Avobenzone 1.0 %

Octocrylene 4.5 %

Oxybenzone 3.0%

Purpose

Sunscreen

Uses

- Helps prevent sunburn
- Higher SPF gives more sunburn protection
- Retains SPF after 80 minutes of activity in the water

WARNINGS:

FOR EXTERNAL USE ONLY.

When using this product

keep out of eyes. Rinse with water to remove.

stop use and ask a doctor if

rash or irritation develops and lasts

KEEP OUT OF REACH OF CHILDREN

keep out of the reach of children. If swallowed get medical help or contact a poison control center right away.

Directions:

apply generously and evenly before sun exposure and as needed

- Children under 6 months of age:ask a doctor
- reapplying frequently after towel drying, swimming or perspiring.

Other Information:

May stain some fabrics.

- Sun Alert: Limiting sun exposure, wearing, protective clothing, and using sunscreens may reduce the risks of skin aging, skin cancer, and other harmful effects of the sun.

INACTIVE INGREDIENTS:

Water, Ethyhexyl Palmitate, Lauryl PEG-8 Dimethicone, Hexyldecanol, Cyclopentasiloxane, Hydrated Silica, Cyclohexasiloxane, Benzyl Alcohol, Acrylates/C12-22 Alkyl Methcrylate Copolymer, Cetyl Dimethicone, Sodium Chloride, Beeswax, Microcrystalline Wax, Polyethylene, PEG-4 Laurate, Stearoxy dimethicone, PEG-4, PEG-8 Dimethicone, Aloe Barbadensis Leaf Juice, OCtyldodecanol, Retinyl Palmitate, Silica, Tocopheryl Acetate, Ascorbic Acid, Sodium Propoxyhydroxypropyl Thiosulfate,Silica, Methylparaben,Propylparaben, Disodium EDTA, Iodopropynyl Butylcarbamate, Fragrance.

Principal Display Panel

PRevail

moisturizing sunscreen

spf 30

- antioxidant-enriched
- uva/uvb protection
- hypoallergic
- oil-free

6.5 FL. OZ. (192 mL)